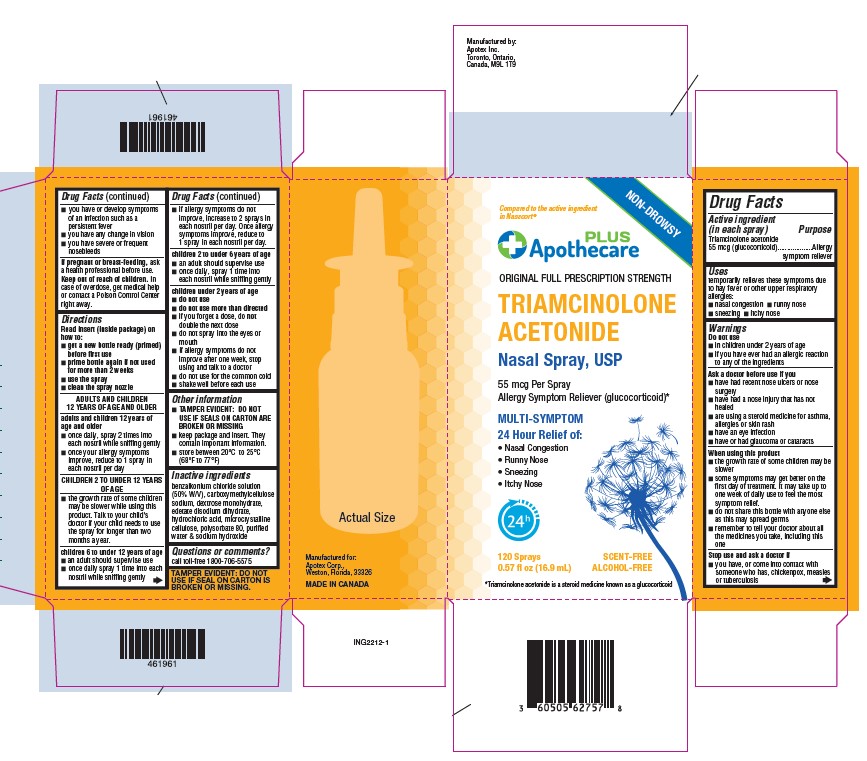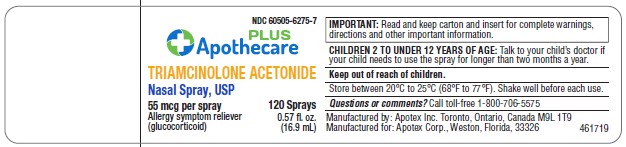 DRUG LABEL: Triamcinolone acetonide
NDC: 60505-6275 | Form: SPRAY, METERED
Manufacturer: Apotex Corp.
Category: otc | Type: HUMAN OTC DRUG LABEL
Date: 20250922

ACTIVE INGREDIENTS: TRIAMCINOLONE ACETONIDE 55 ug/1 1
INACTIVE INGREDIENTS: BENZALKONIUM CHLORIDE; DEXTROSE MONOHYDRATE; EDETATE DISODIUM; HYDROCHLORIC ACID; SODIUM HYDROXIDE ; WATER ; MICROCRYSTALLINE CELLULOSE; POLYSORBATE 80 ; CARBOXYMETHYLCELLULOSE SODIUM, UNSPECIFIED

Drug Facts

Active ingredient (in each spray)

Triamcinolone acetonide 55 mcg (glucocorticoid)

Purpose

Allergy symptom reliever

Uses

Temporarily relieves these symptoms of hey fever or other respiratory allergies:

- nasal congestion
- runny nose
- sneezing
- itchy nose

Warnings

For external use only

Do not use

- In children under 2 years of age
- If you have ever had an allergic reaction to any of the ingredients

Ask a doctor before use if you

- have had recent nose ulcers or nose surgery
- have had a nose injury that has not healed
- are using a steroid medicine for asthma, allergies or skin rash
- have an eye infection
- have or had glaucoma or cataracts

When using this product

- the growth rate of some children may be slower
- some symptoms may get better on the first day of treatment. It may take up to one week of daily use to feel the most symptom relief.
- do not share this bottle with anyone else as this may spread germs
- remember to tell your doctor about all the medicines you take, including this one

Stop use and ask a doctor if

- you have, or come in contact with someone who has, chickenpox, measles or tuberculosis
- you have or develop symptoms of an infection such as persist fever
- you have any change in vision
- you have severe or frequent nosebleeds

If pregnant or breast-feeding,

ask a health professional before use.

Keep out of reach of children.

In case of overdose, get medical help or contact a Poison Control Center right away.

Directions

Read insert (inside package) on how to:

- get a new bottle ready (primed) before first use
- prime bottle again if not used for more than 2 weeks
- use the spray
- clean the spray nozzle
  ADULTS AND CHILDREN 12 YEARS OF AGE AND OLDER
  adults and children 12 years of age and older | - once daily, spray 2 times into each nostril while sniffing gently
  adults and children 12 years of age and older | - once your allergy symptoms improve, reduce to 1 spray in each nostril
  CHILDREN 2 TO UNDER 12 YEARS OF AGE
  - the growth rate of some children may be slower while using this product. Talk to your child’s doctor if your child needs to use the spray longer than two months a year.
  children 6 to under 12 years of age | - an adult should supervise use
  children 6 to under 12 years of age | - once daily, spray 1 time into each nostril while sniffing gently
  children 6 to under 12 years of age | - if allergy symptoms do not improve, increase to 2 sprays in each nostril per day. Once allergy symptoms improve, reduce to 1 spray in each nostril per day.
  children 2 to under 6 years of age | - an adult should supervise use
  children 2 to under 6 years of age | - once daily, spray 1 time into each nostril while sniffing gently
  children under 2 years of age | - do not use

- do not use more than directed
- if you forget a dose, do not double the next dose
- do not spray into eyes or mouth
- if allergy symptoms do not improve after one week, stop using and talk to a doctor
- do not use for the common cold
- shake well before each use

Other information

- TAMPER EVIDENT: DO NOT USE IF SEALS ON CARTON ARE BROKEN OR MISSING
- Store between 20ºC to 25ºC (68ºF to 77ºF)

Inactive ingredients

benzalkonium chloride solution (50% W/V) dextrose monohydrate, edetate disodium dihydrate, hydrochloric acid, microcrystalline cellulose, polysorbate 80 purified water & sodium hydroxide

Questions or comments?

Call toll-free1-800-706-5575

Principal Display Panel

Triamcinolone Acetonide Nasal Spray, USP

55 mcg per spray

allergy symptom reliever (glucocorticoid)

120 MD per spray

NDC 60505-6275-7